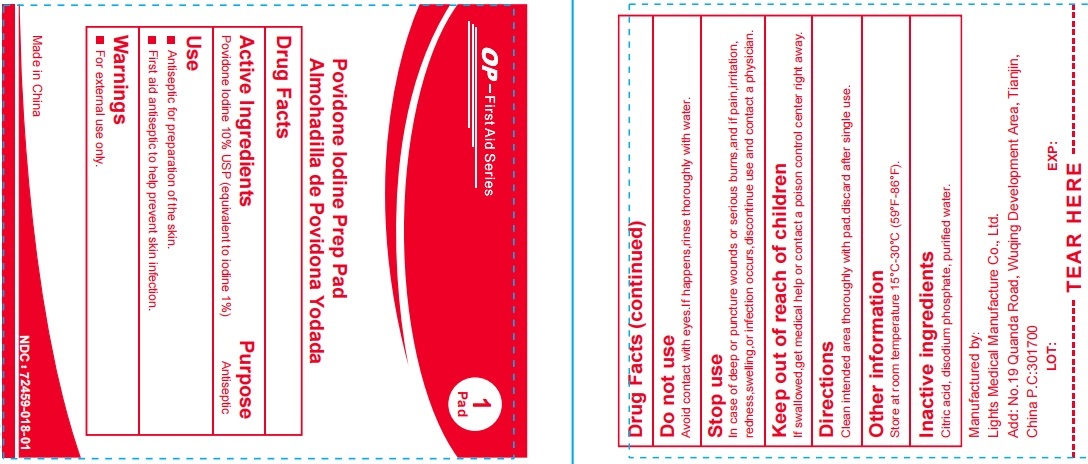 DRUG LABEL: Op-First Aid Series Povidone Iodine Prep Pad
NDC: 72459-018 | Form: SOLUTION
Manufacturer: Yiwu Ori-Power Medtech Co.,Ltd.
Category: otc | Type: HUMAN OTC DRUG LABEL
Date: 20250529

ACTIVE INGREDIENTS: POVIDONE-IODINE 1 g/100 g
INACTIVE INGREDIENTS: WATER; CITRIC ACID MONOHYDRATE; SODIUM PHOSPHATE, DIBASIC

Op-First Aid Series Povidone Iodine Prep Pad

Active Ingredient: Povidone-Iodine 10% USP (equivalent to iodine 1%)

Purpose: Antiseptic

Use

- Antiseptic for preparation of the skin.
- First aid antiseptic to help prevent skin infection.

Warnings:

- For external use only

Keep out of reach of children

If swallowed get medical help or contact a poison control center right away.

Stop use

In case of deep or puncture wounds or serious burns and if pain, irritation, redness, swelling, or infection occurs, discontinue use and contact a physician.

Directions

Clean intended area thoroughly with pad, discard after single use.

Other information

Store at room temperature 15ºC-30ºC (59ºF-86ºF)

Inactive Ingredients

Citric acid, disodiumphosphate, purified water.